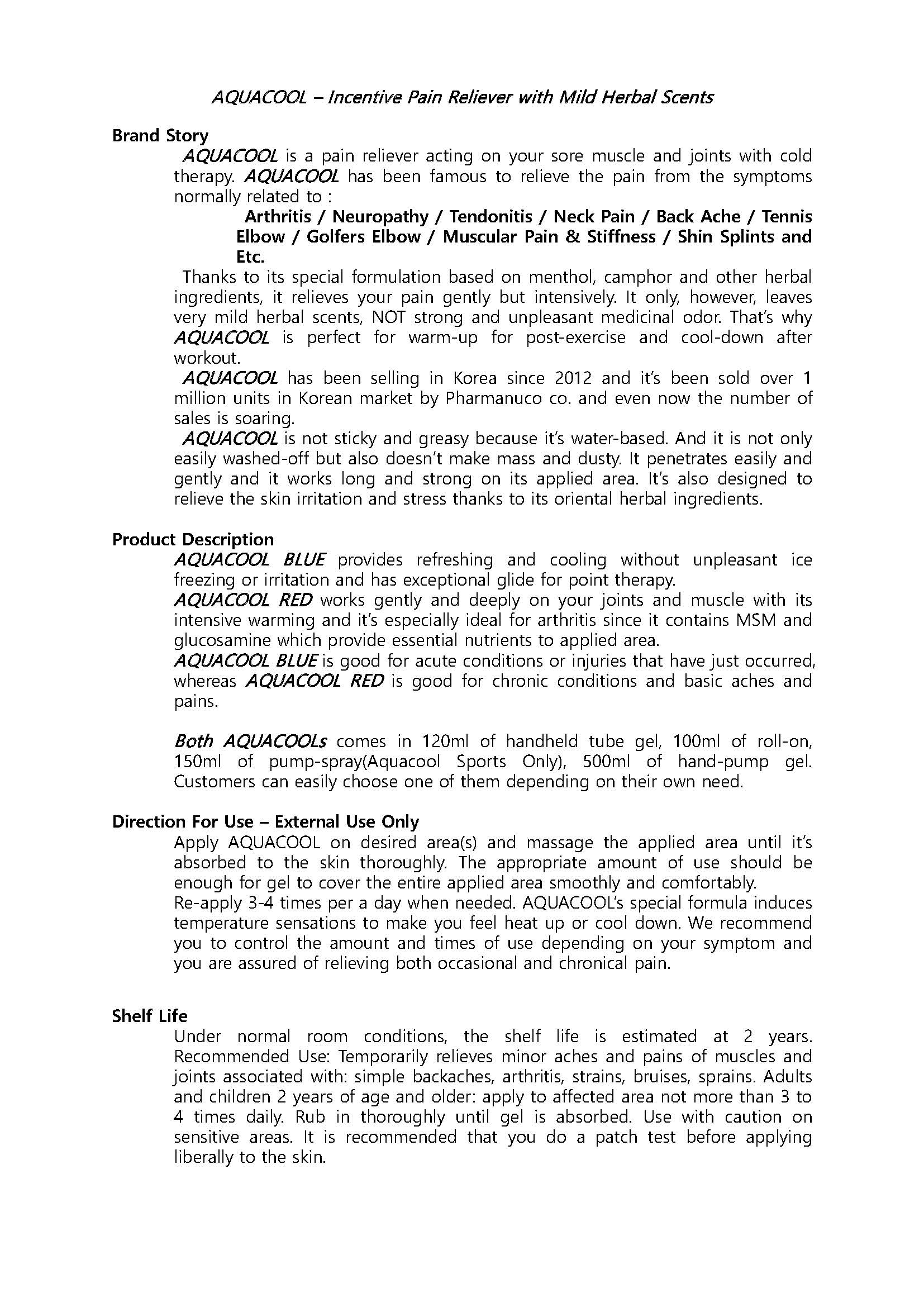 DRUG LABEL: AQUACOOL
NDC: 70759-0004 | Form: SPRAY
Manufacturer: Pharmanuco
Category: otc | Type: HUMAN OTC DRUG LABEL
Date: 20210309

ACTIVE INGREDIENTS: MENTHOL 5 g/100 mL
INACTIVE INGREDIENTS: WATER; GLYCERIN; ALLANTOIN

Drug Facts

ACTIVE INGREDIENT

MENTHOL

INACTIVE INGREDIENT

ALCOHOL, WATER, GLYCERIN, EUCALYPTUS GLOBULUS LEAF OIL, GLYCYRRHIZA (LICORICE) ROOT EXTRACT, BOSWELLIA SERRATA GUM EXTRACT, ALLANTOIN

PURPOSE

To relieve pain

keep out of reach of the children

INDICATIONS AND USAGE

Spray proper amount to treatment area(s)

DOSAGE AND ADMINISTRATION

for external use only

WARNINGS

1. Under normal room conditions, the shelf life is estimated at 2 years.
2. Recommended Use: Temporarily relieves minor aches and pains of muscles and joints associated with: simple backaches, arthritis, strains, bruises, sprains.
3. Adults and children 2 years of age and older: apply to affected area not more than 3 to 4 times daily.
4. Rub in thoroughly until gel is absorbed.
5. Use with caution on sensitive areas.
6. It is recommended that you do a patch test before applying liberally to the skin.